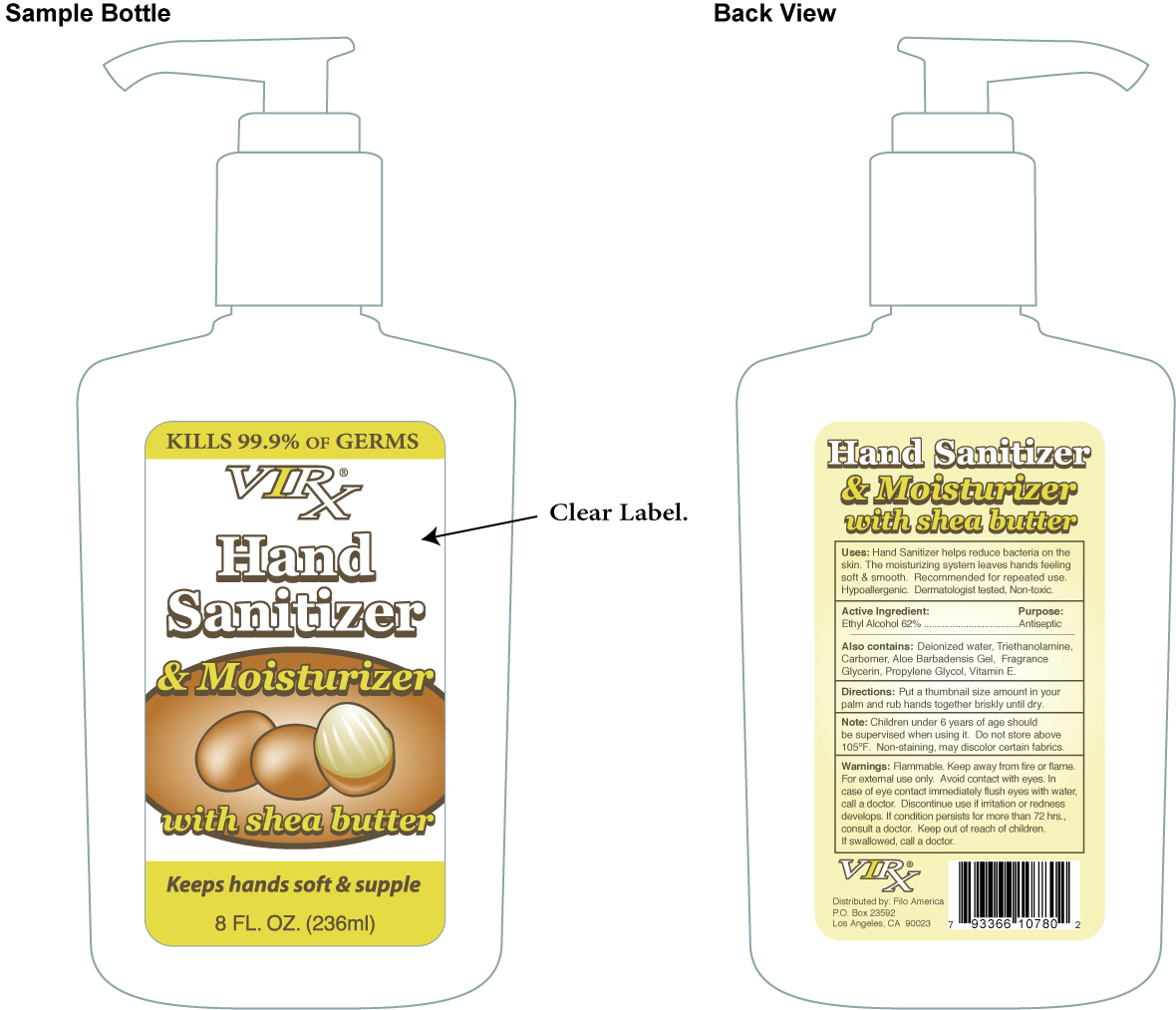 DRUG LABEL: Virx
NDC: 40104-811 | Form: LOTION
Manufacturer: Ningbo Pulisi Daily Chemical Products
Category: otc | Type: HUMAN OTC DRUG LABEL
Date: 20091123

ACTIVE INGREDIENTS: Alcohol 154 mL/236 mL
INACTIVE INGREDIENTS: Water; Trolamine; Carbomer 934; Aloe Vera Leaf; Glycerin; Alpha-tocopherol; Propylene Glycol 

Virx Hand Sanitizer & Moisturizer with Shea Butter

INDICATIONS AND USAGE

Directions: Put a thumbnail size amount in your palm and rub hands together briskly until dry.

ACTIVE INGREDIENT

Ethyl Alcohol 62%.......................................................................Antiseptic

KEEP OUT OF REACH OF CHILDREN

Note. Children under 6 years of age should be supervised when using it. Do not store above 105 degrees F. Non-staining, may discolor fabrics.

WARNINGS

Warnings: Flammable. Keep away from fire or flame. For external use only. Avoid contact with eyes. In case of eye contact immediately flush eyes with water, call a doctor. Discontinue use if irritation or redness develops. If condition persists for more than 72 hours, consult a doctor. Keep out of reach of children. If swallowed, call a doctor.

INACTIVE INGREDIENT

Also contains: Deionized water, Triethanolamine, Carbomer, Aloe Barbadensis Gel, Fragrance, Glycerin, Propylene Glycol, Vitamin E.

PURPOSE

Uses: Hand Sanitizer helps reduce bacteria on the skin. The moisturizing system leaves hands feeling soft and smooth. Recommended for repeated use. Hypoallergenic. Dematologist tested, non-toxic.

PACKAGE LABEL

MM1